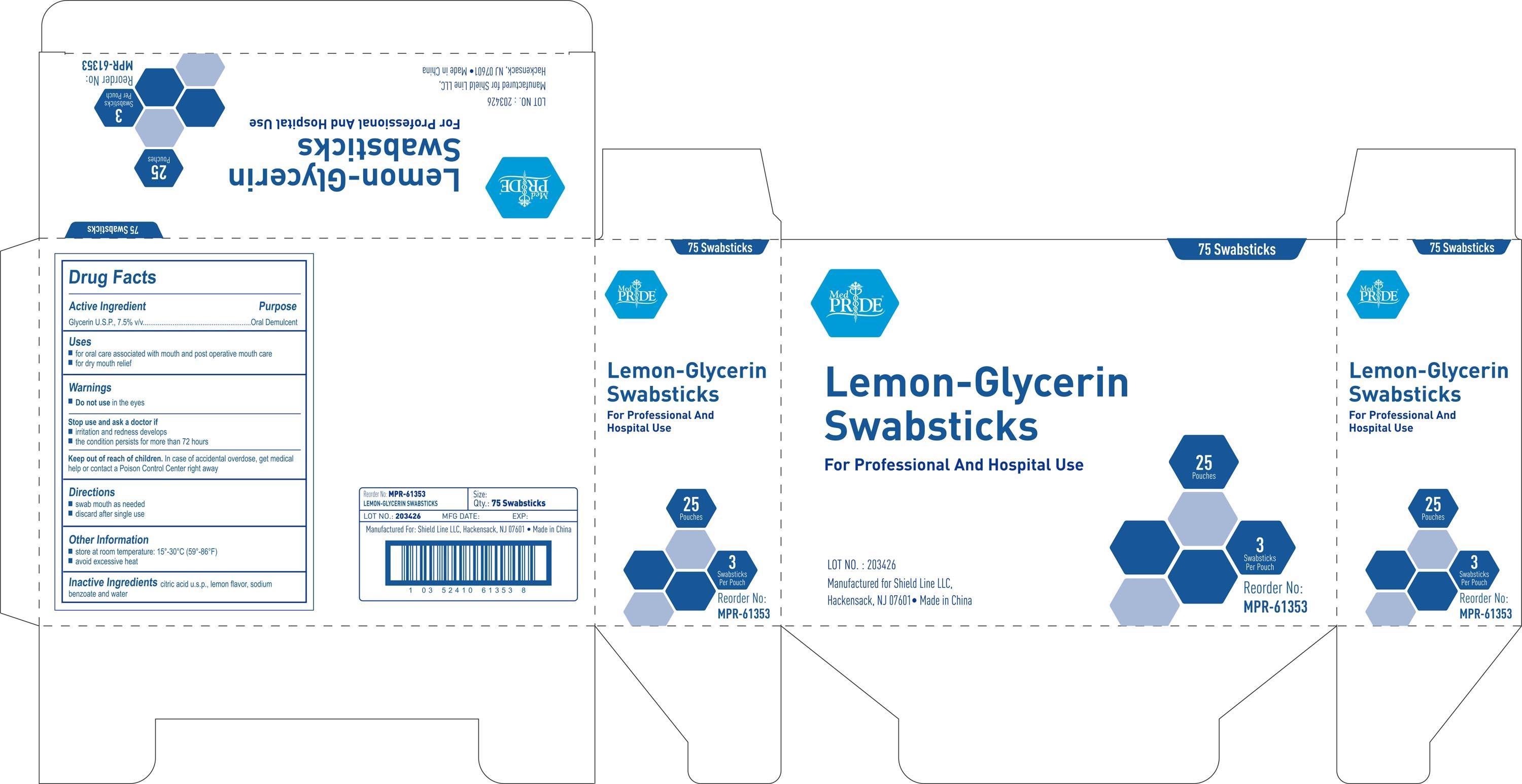 DRUG LABEL: MedPride
NDC: 52410-6135 | Form: SWAB
Manufacturer: Shield Line LLC
Category: otc | Type: HUMAN OTC DRUG LABEL
Date: 20140506

ACTIVE INGREDIENTS: GLYCERIN 0.075 g/1 1
INACTIVE INGREDIENTS: CITRIC ACID MONOHYDRATE; SODIUM BENZOATE; WATER

Drug Facts

Active Ingredient

Glycerin U.S.P., 7.5% v/v

Purpose

Oral Demulcent

Uses

■ for oral care associated with mouth and post operative mouth care

■ for dry mouth relief

Warnings

■ Do not use in the eyes

Stop use and ask a doctor if

■ irritation and redness develops

■ the condition persists for more than 72 hours

Keep out of reach of children

In case of accidental overdose, get medical help or contact a Poison Control Center right away.

Directions

■ swab mouth as needed

■ discard after single use

Other Information

■ store at room temperature:15-30C (59-86F)

■ avoid excessive heat

Inactive Ingredients

citric acid u.s.p., lemon flavor, sodium benzoate and water